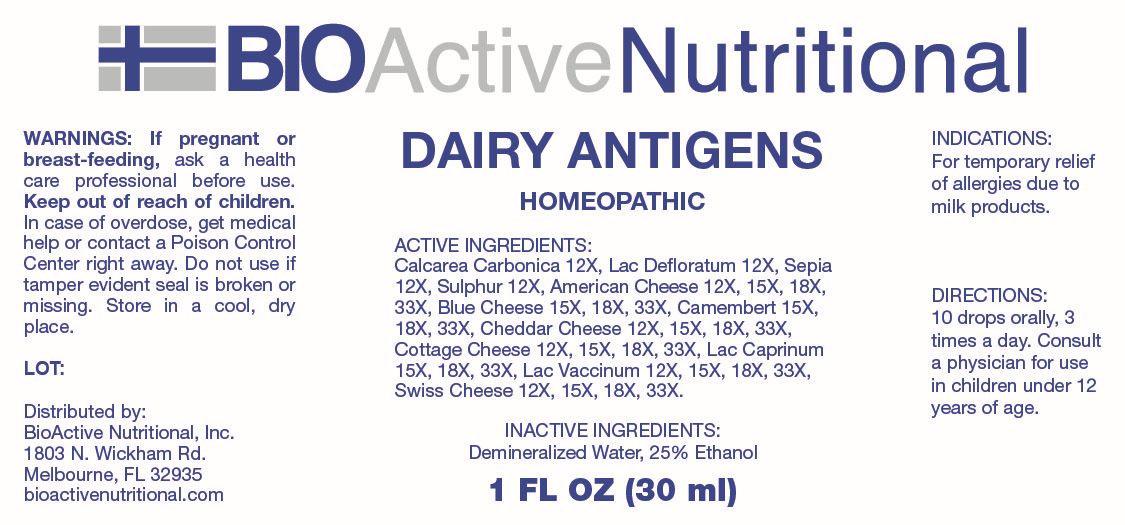 DRUG LABEL: Dairy Antigens
NDC: 43857-0803 | Form: LIQUID
Manufacturer: BioActive Nutritional
Category: homeopathic | Type: HUMAN OTC DRUG LABEL
Date: 20260120

ACTIVE INGREDIENTS: OYSTER SHELL CALCIUM CARBONATE, CRUDE 12 [hp_X]/1 mL; SKIM MILK 12 [hp_X]/1 mL; SEPIA OFFICINALIS JUICE 12 [hp_X]/1 mL; SULFUR 12 [hp_X]/1 mL; WHEY 15 [hp_X]/1 mL; CASEIN, LACTOCOCCUS LACTIS CULTURED, PENICILLIUM ROQUEFORTI CULTURED, AGED 15 [hp_X]/1 mL; CASEIN, LACTOCOCCUS LACTIS CULTURED, PENICILLIUM CAMEMBERTI CULTURED, AGED 15 [hp_Q]/1 mL; CASEIN, LACTOCOCCUS LACTIS CULTURED, AGED 12 [hp_X]/1 mL; CASEIN, LACTOCOCCUS LACTIS CULTURED 12 [hp_X]/1 mL; GOAT MILK 15 [hp_X]/1 mL; COW MILK 12 [hp_X]/1 mL; CASEIN, EMMENTAL CULTURED 12 [hp_X]/1 mL
INACTIVE INGREDIENTS: WATER; ALCOHOL

DRUG FACTS:

ACTIVE INGREDIENTS:

Calcarea Carbonica 12X, Lac Defloratum 12X, Sepia 12X, Sulphur 12X, American Cheese 12X, 15X, 18X, 33X, Blue Cheese 15X, 18X, 33X, Camembert 15X, 18X, 33X, Cheddar Cheese 12X, 15X, 18X, 33X, Cottage Cheese 12X, 15X, 18X, 33X, Lac Caprinum 15X, 18X, 33X, Lac Vaccinum 12X, 15X, 18X, 33X, Swiss Cheese 12X, 15X, 18X, 33X.

PURPOSE:

For temporary relief of allergies due to milk products.

WARNINGS:

If pregnant or breast-feeding, ask a health care professional before use.

Keep out of reach of children. In case of overdose, get medical help or contact a Poison Control Center right away.

Do not use if tamper evident seal is broken or missing.

Store in a cool, dry place.

KEEP OUT OF REACH OF CHILDREN:

In case of overdose, get medical help or contact a Poison Control Center right away.

DIRECTIONS:

10 drops orally, 3 times a day. Consult a physician for use in children under 12 years of age.

INDICATIONS:

For temporary relief of allergies due to milk products.

INACTIVE INGREDIENTS:

Demineralized Water, 25% Ethanol

QUESTIONS:

Distributed by:

BioActive Nutritional, Inc.

1803 N. Wickham Rd.

Melbourne, FL 32935

bioactivenutritional.com

PACKAGE LABEL DISPLAY:

BIOActiveNutritional

DAIRY ANTIGENS

HOMEOPATHIC

1 FL OZ (30 ml)